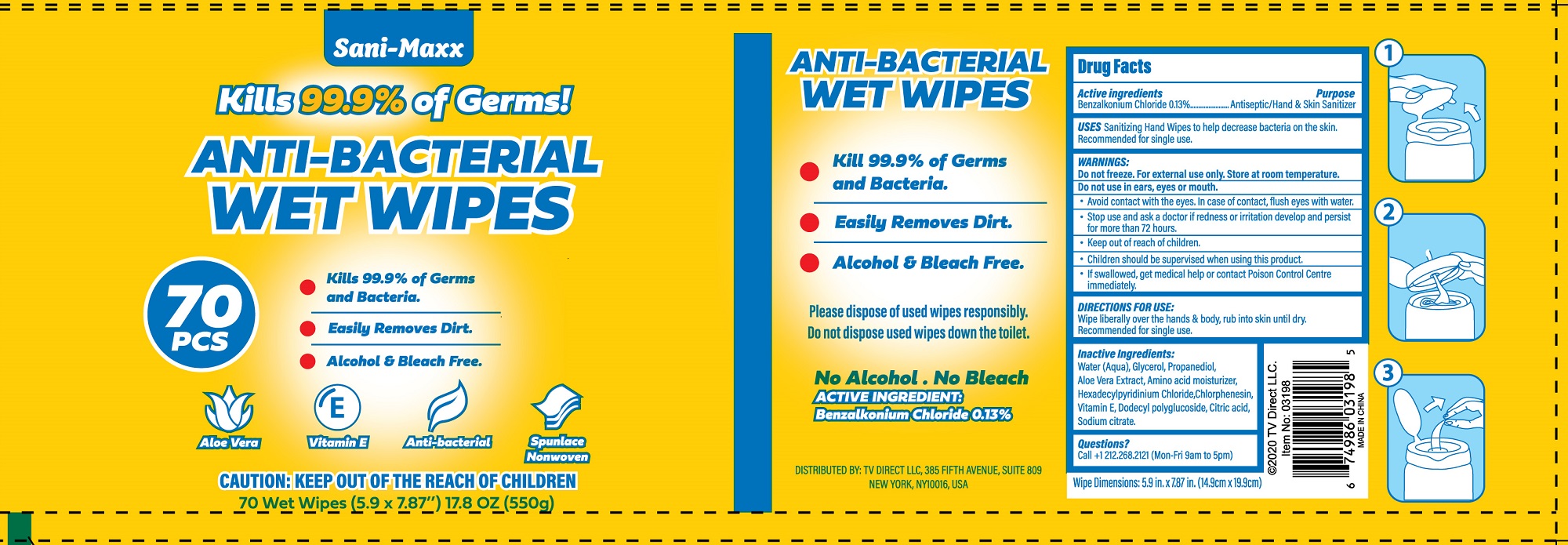 DRUG LABEL: ANTI-BACTERIAL WET WIPES
NDC: 78028-004 | Form: CLOTH
Manufacturer: Dalian Daxin Nonwoven Technology Co., Ltd.
Category: otc | Type: HUMAN OTC DRUG LABEL
Date: 20220114

ACTIVE INGREDIENTS: BENZALKONIUM CHLORIDE 0.13 g/100 g
INACTIVE INGREDIENTS: SODIUM CITRATE; .ALPHA.-TOCOPHEROL; GLYCERIN; ALOE VERA LEAF; POLY(LAURYLGLUCOSIDE)-7; PROPANEDIOL; BETAINE; CETYLPYRIDINIUM CHLORIDE ANHYDROUS; CHLORPHENESIN; WATER; CITRIC ACID MONOHYDRATE

78028-004 ANTI-BACTERIAL WET WIPES 0.13% BENZALKONIUM CHLORIDE

Active Ingredient

Benzalkonium Chloride 0.13%

Purpose

Antiseptic/Hand & Skin Sanitizer

USE

Sanitizing Hand Wipes to help decrease bacteria on the skin.
Recommended for single use.

WARNINGS

Do not freeze. For external use only, Store at room temperature.
Do not use in ears, eyes or mouth.
Avoid contact with the eyes. In case of contact, flush eyes with water.
Stop use and ask a doctor if redness or irritation develop and persist
for more than 72 hours,

●Keep out of reach of children.
●Children should be supervised when using this product.
If swallowed, get medical help or contact Poison Control Centre
immediately.

Directions

Wipe liberally over the hands & body, rub into skin until dry,
Recommended for single use.

Inactive ingredients

Water (Aqua), Glycerol, Propanediol,
Aloe Vera Extract, Amino acid moisturizer,
Hexadecylpyridinium Chloride,Chlorphenesin,
Vitamin E, Dodecyl polyglucoside, Citric acid,
Sodium citrate.